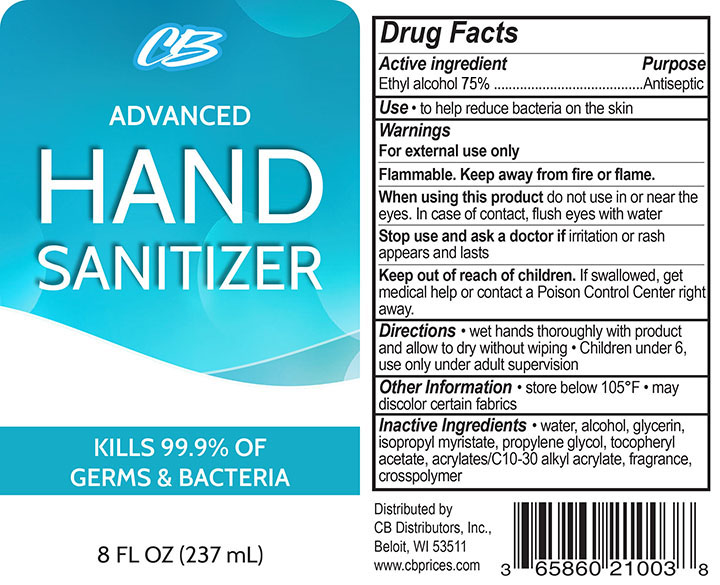 DRUG LABEL: CB Advanced Hand Sanitizer
NDC: 73529-353 | Form: GEL
Manufacturer: Nutritech Pharmaceuticals, Inc
Category: otc | Type: HUMAN OTC DRUG LABEL
Date: 20200504

ACTIVE INGREDIENTS: ALCOHOL 75 mL/100 mL
INACTIVE INGREDIENTS: ALOE VERA LEAF; CARBOMER HOMOPOLYMER, UNSPECIFIED TYPE; TROLAMINE; WATER; .ALPHA.-TOCOPHEROL; GLYCERIN

Active Ingredients

Ethyl alcohol 75%

Purpose

Antiseptic

Uses

Hand sanitizer

Warnings

For external use only.

When using this product, do not use in or near the eyes, ln case of contact, rinse eyes thoroughly with water.

Discontinue if irritation or redness develops. If condition persists for more than 72 hours, consult a doctor.

Keep out of reach of children. If swallowed, get medical help or contact a Poison Control Center right away

Directions

Place enough product in palm to cover hands and rub hands together briskly until dry.

Inactive Ingredients

Purified Water, Glycerin, Triethanolamine, Carbomer fragrance, Vitamin E, Aloe Vera.

Made in China